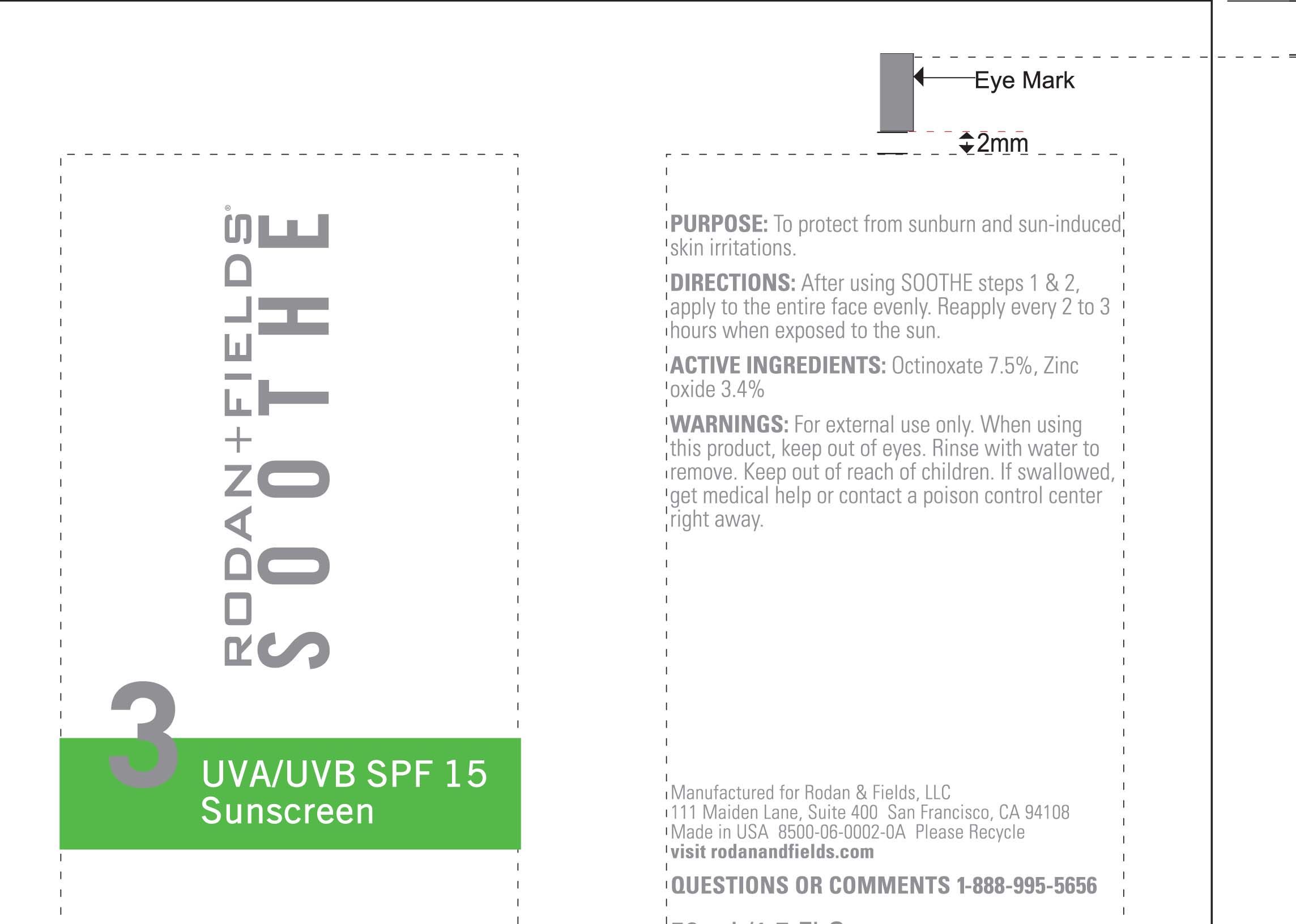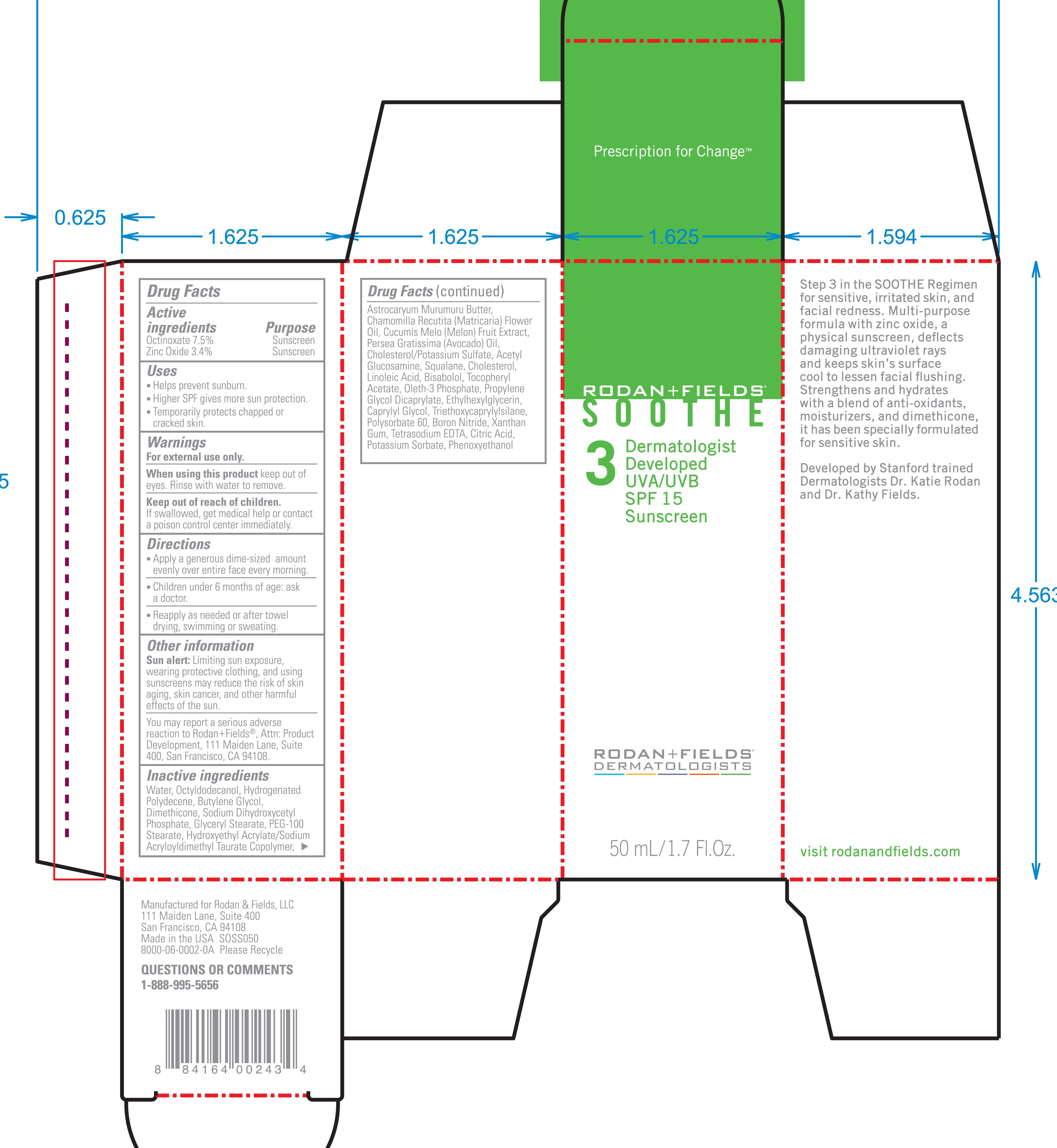 DRUG LABEL: UVA/UVB SPF 15 
NDC: 14222-2022 | Form: LOTION
Manufacturer: Rodan & Fields LLC.
Category: otc | Type: HUMAN OTC DRUG LABEL
Date: 20120124

ACTIVE INGREDIENTS: OCTINOXATE 7.5 mL/100 mL; ZINC OXIDE 3.4 mL/100 mL
INACTIVE INGREDIENTS: WATER; OCTYLDODECANOL; HYDROGENATED POLYDECENE (550 MW); BUTYLENE GLYCOL; DIMETHICONE; GLYCERYL MONOSTEARATE; PEG-100 STEARATE; ASTROCARYUM MURUMURU SEED BUTTER; CHAMOMILE FLOWER OIL; CANTALOUPE; SQUALENE; CHOLESTEROL; OLETH-3 PHOSPHATE

UVA and UVB SPF 15 Sunscreen

Active Ingredients Purpose

Octinoxate 7.5% Sunscreen

Zinc Oxide 3.4% Sunscreen

Uses
Helps prevent sunburn
Higher SPF gives more sun protection
Temporarily protects chapped or cracked skin.

Keep out of reach of children. If swallowed get medical help or contact a Poison Control Center immediately.

when using this product keep out of eyes. Rinse with water to remove.

Directions

Apply a generous dime-sized amount evenly over entire face every morning

Children under 6 months of age: ask a doctor.

Reapply as needed or after towel drying, swimming, or sweating.

INACTIVE INGREDIENT

Water, Octyldodecanol, Hydrogenated polydecene, butylene glycol, dimethicone, sodium dihydroxycetyl phosphate, glyceryl stearate, PEG-100 stearate, hydroxyethyl acrylate/sodium acryloyldimethyl taurate copolymer, astrocaryum murumuru butter, Chamomilla recutita (matricaria) flower oil, Cucumis melo (melon) fruit extract, Persea Gratissima (avacado) oil, Cholesterol/Potassium sulfate, Acetyl glucosamine, squalene, Cholesterol, Linoleic acid, Bisabolol, Tocopheryl Acetate, Oleth-3 phosphate, propylene glycol dicaprylate ethylhexylglycerin, caprylyl glycol, triethoxycaprylylsilane, polysorbate 60, boron nitride, xanthan gum, tetrasodium EDTA, citric acid, potassium sorbate, phenoxyethanol

PACKAGE LABEL

Rodan and Fields

Soothe

UVA/UVB SPF 15 Sunscreen
50 mL/ 1.7 Fl. Oz.